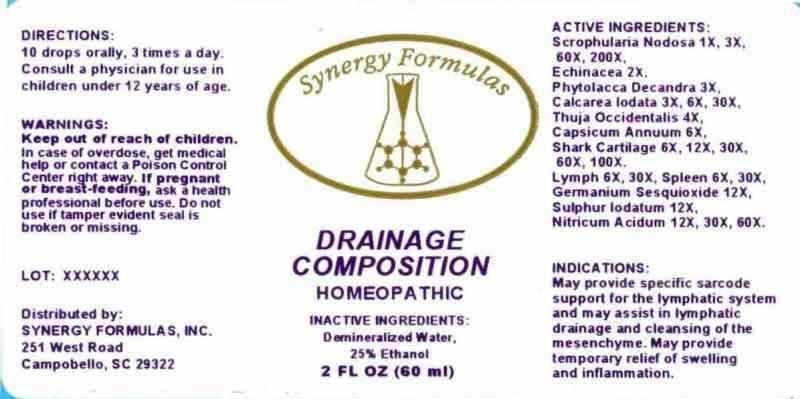 DRUG LABEL: Drainage Composition
NDC: 43772-0034 | Form: LIQUID
Manufacturer: Synergy Formulas, Inc.
Category: homeopathic | Type: HUMAN OTC DRUG LABEL
Date: 20140602

ACTIVE INGREDIENTS: SCROPHULARIA NODOSA 1 [hp_X]/1 mL; ECHINACEA ANGUSTIFOLIA 2 [hp_X]/1 mL; PHYTOLACCA AMERICANA ROOT 3 [hp_X]/1 mL; CALCIUM IODIDE 3 [hp_X]/1 mL; THUJA OCCIDENTALIS LEAFY TWIG 4 [hp_X]/1 mL; CAPSICUM 6 [hp_X]/1 mL; SHARK CARTILAGE 6 [hp_X]/1 mL; SUS SCROFA LYMPH 6 [hp_X]/1 mL; SUS SCROFA SPLEEN 6 [hp_X]/1 mL; GERMANIUM SESQUIOXIDE 12 [hp_X]/1 mL; SULFUR IODIDE 12 [hp_X]/1 mL; NITRIC ACID 12 [hp_X]/1 mL
INACTIVE INGREDIENTS: WATER; ALCOHOL

Drug Facts

ACTIVE INGREDIENTS:

Scrophularia nodosa 1X, 3X, 60X, 200X, Echinacea (Angustifolia) 2X, Phytolacca decandra 3X, Calcarea iodata 3X, 6X, 30X, Thuja occidentalis 4X, Capsicum annuum 6X, Shark cartilage 6X, 12X, 30X, 60X, 100X, Lymph (suis) 6X, 30X, Spleen (suis) 6X, 30X, Germanium sesquioxide 12X, Sulphur iodatum 12X, Nitricum acidum 12X, 30X, 60X.

INDICATIONS:

May provide specific sarcode support for the lymphatic system and may assist in lymphatic drainage and cleansing of the mesenchyme. May provide temporary relief of swelling and inflammation.

WARNINGS:

Keep out of reach of children. In case of overdose, get medical help or contact a Poison Control Center right away.

If pregnant or breast-feeding, ask a health professional before use.

Do not use if tamper evident seal is broken or missing.

Keep out of reach of children. In case of overdose, get medical help or contact a Poison Control Center right away.

DIRECTIONS:

10 drops orally, 3 times a day. Consult a physician for use in children under 12 years of age.

INDICATIONS:

May provide specific sarcode support for the lymphatic system and may assist in lymphatic drainage and cleansing of the mesenchyme. May provide temporary relief of swelling and inflammation.

INACTIVE INGREDIENTS:

Demineralized Water, 25% Water

QUESTIONS:

Distributed by:

SYNERGY FORMULAS, INC.

251 West Road

Campobello, SC 29312

PACKAGE LABEL DISLPAY:

Synergy Formulas

DRAINAGE COMPOSITION

HOMEOPATHIC

2 FL OZ (60 ml)